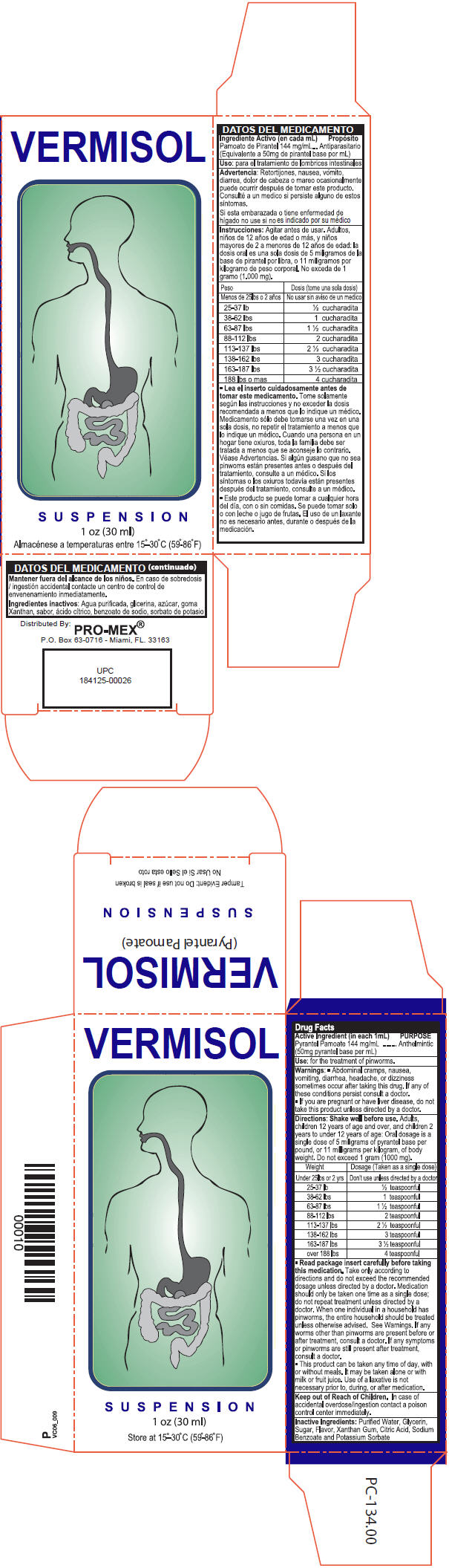 DRUG LABEL: Pyrantel Pamoate
NDC: 58988-1770 | Form: SUSPENSION
Manufacturer: ProMex LLC
Category: otc | Type: HUMAN OTC DRUG LABEL
Date: 20241218

ACTIVE INGREDIENTS: Pyrantel Pamoate 144 mg/1 mL
INACTIVE INGREDIENTS: Water; Citric Acid Monohydrate; Glycerin; Sucrose; Xanthan Gum; Sodium Benzoate; Potassium Sorbate

Pyrantel Pamoate

Drug Facts

Active Ingredient (in each 1mL)

Pyrantel Pamoate 144 mg/mL
(50mg pyrantel base per mL)

Purpose

Anthelmintic

Use

for the treatment of pinworms.

Warnings

ASK DOCTOR

*Abdominal cramps, nausea, vomiting, diarrhea, headache, or dizziness sometimes occurs after taking this drug. If any of these conditions persist, consult a doctor.

PREGNANCY OR BREAST FEEDING

*If you are pregnant or have liver disease, do not take this product unless directed by a doctor.

Directions

Shake well before use. Adults, children 12 years of age and over, and children 2 years to under 12 years of age: Oral dosage is a single dose of 5 milligrams of pyrantel base per pound, or 11 milligrams per kilogram, of body weight. Do not exceed 1 gram (1000 mg).

Weight | Dosage (Taken as a single dose)
Under 25 lbs or 2 yrs. | Don't use unless directed by a doctor
25-37 lbs | ½ teaspoonful
38-62 lbs | 1 teaspoonful
63-87 lbs | 1 ½ teaspoonful
88-112 lbs | 2 teaspoonful
113-137 lbs | 2 ½ teaspoonful
138-162 lbs | 3 teaspoonful
163-187lbs | 3 ½ teaspoonful
over 188 lbs | 4 teaspoonful

*Read package insert carefully before taking this medication. Take only according to directions and do not exceed the recommended dosage unless directed by a doctor. Medication should only be taken one time as a single dose; do not repeat treatment unless directed by a doctor. When one individual in a household has pinworms, the entire household should be treated unless otherwise advised. See Warnings. If any worms other than pinworms are present before or after treatment consult a doctor. If any symptoms or pinworms are still present after treatment, consult a doctor.

*This product can be taken any time of day, with or without meals, it may be taken alone or with milk or fruit juice. Use of a laxative is not necessary prior to, during or after medication.

Keep out of Reach of Children. In case of accidental overdose/ingestion contact a poison control center immediately.

Inactive Ingredients

Purified Water, Glycerin, Sugar, Flavor, Xanthan Gum, Citric Acid, Sodium Benzoate and Potassium Sorbate

PRINCIPAL DISPLAY PANEL - 30 ml Bottle Carton

VERMISOL

SUSPENSION

1 oz (30 ml)